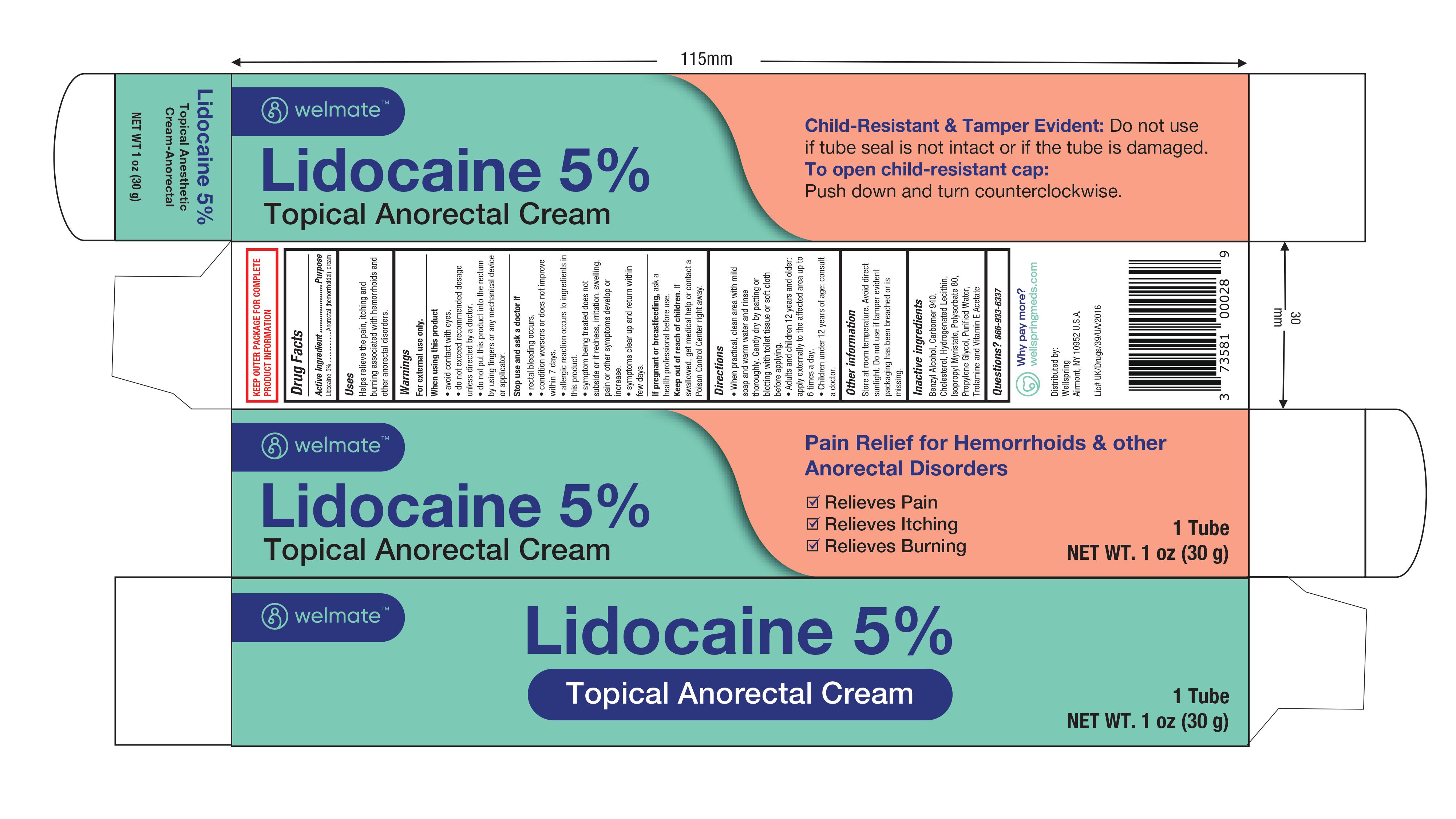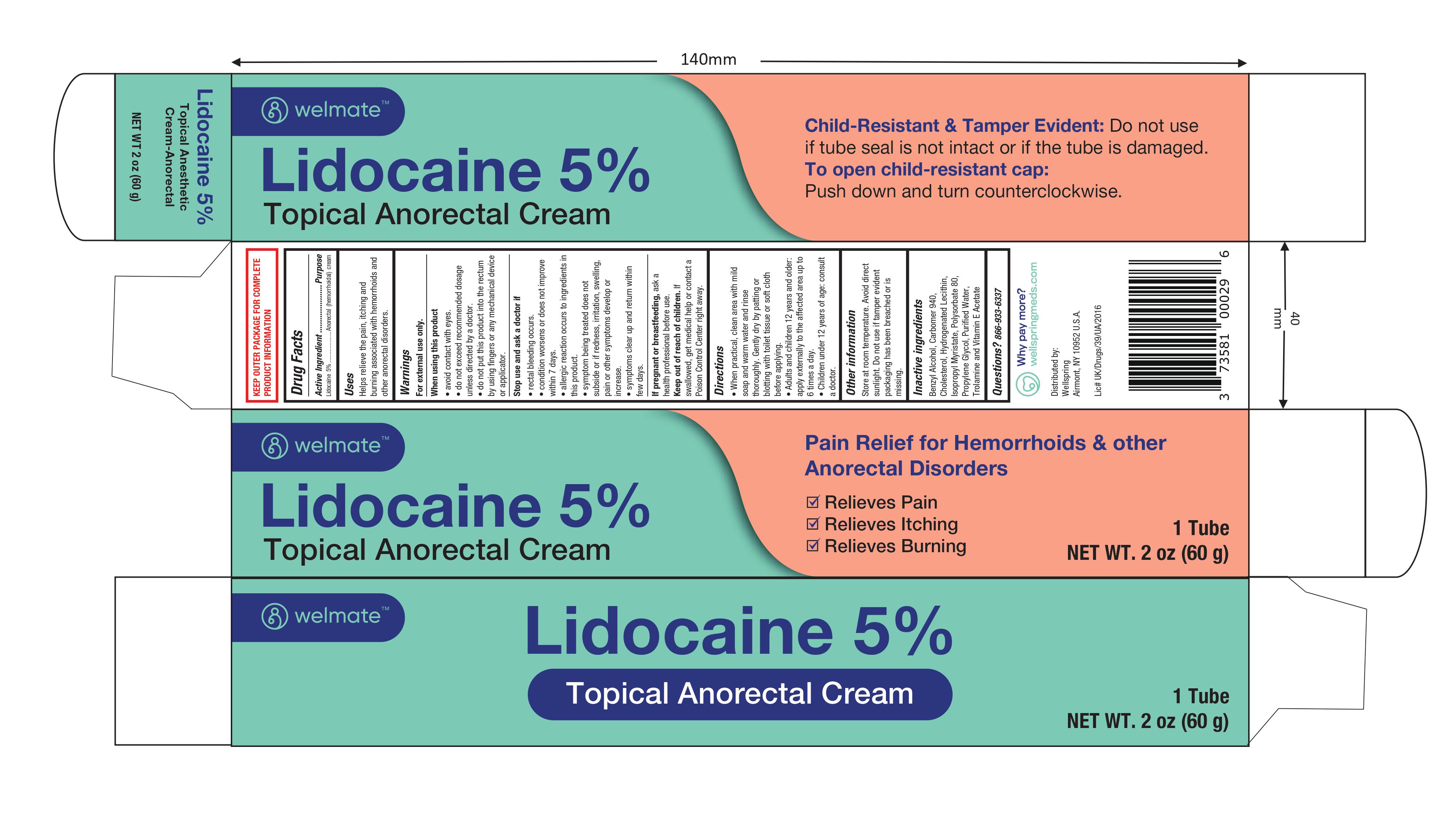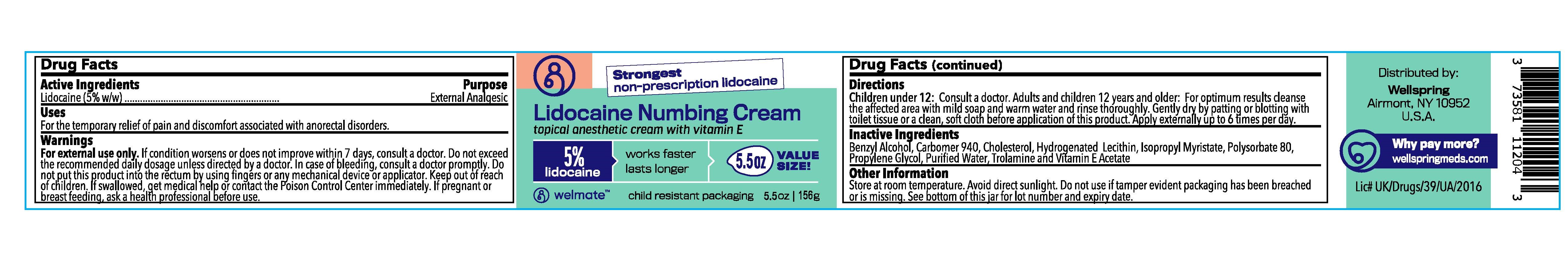 DRUG LABEL: Lidocaine Numbing Cream
NDC: 73581-105 | Form: CREAM
Manufacturer: Yyba Corp
Category: otc | Type: HUMAN OTC DRUG LABEL
Date: 20241106

ACTIVE INGREDIENTS: LIDOCAINE 50 mg/1 mL
INACTIVE INGREDIENTS: BENZYL ALCOHOL; CARBOMER 940; CHOLESTEROL; LECITHIN, SOYBEAN; ISOPROPYL MYRISTATE; POLYSORBATE 80; PROPYLENE GLYCOL; WATER; TROLAMINE; .ALPHA.-TOCOPHEROL ACETATE

Lidocaine Numbing Cream topical anesthetic cream with vitamin E

Active Ingredient:

Lidocaine HCl 5.0%

Purpose

- External Analgesic

Uses:

For the temporary relief of pain and discomfort associated with anorectal disorders.

Warnings:

- For external use only. If condition worsens or does not improve within 7 days, consult a doctor.

When using this product,

- Do not exceed the recommended daily dosage unless directed by a doctor.
- In case of bleeding, consult a doctor promptly.
- Do not put this product into the rectum by using ﬁngers or any mechanical device or applicator.
- Keep out of reach of children.
- If swallowed, get medical help or contact the Poison Control Center immediately.
- If pregnant or breast feeding, ask a health professional before use.

Directions:

Children under 12: Consult a doctor.

Adults and children 12 years and older: For optimum results cleanse the affected area with mild soap and warm water and rinse thoroughly. Gently dry by patting or blotting with toilet tissue or a clean, soft cloth before application of this product. Apply externally up to 6 times per day.

Inactive Ingredients

Benzyl Alcohol, Carbomer 940, Cholesterol, Hydrogenated Lecithin, Isopropyl Myristate, Polysorbate 80, Propylene Glycol, Puriﬁed Water, Trolamine and Vitamin E Acetate

Other Information:

Store at room temperature. Avoid direct sunlight. Do not use if tamper evident packaging has been breached or is missing. See bottom of this jar for lot number and expiry date.

Distributed by: Wellspring Airmont, NY 10952 U.S.A.